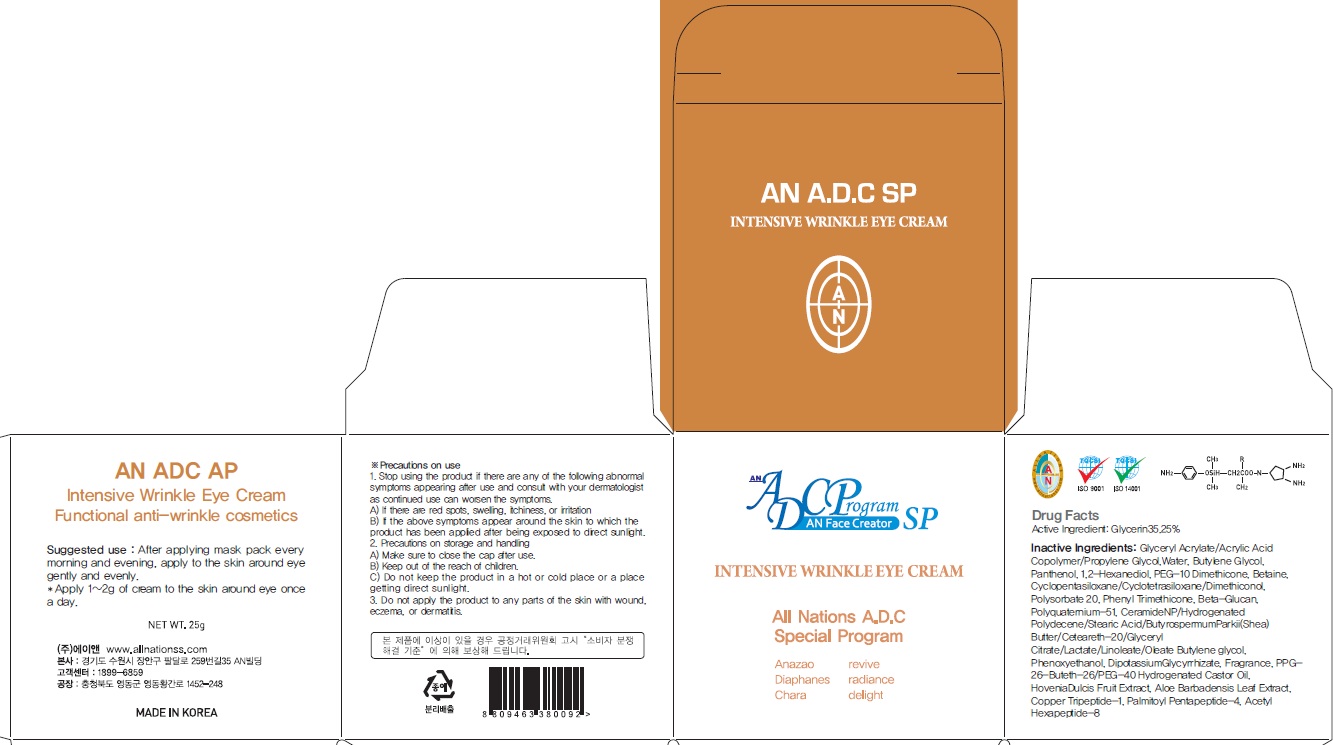 DRUG LABEL: AN ADC SP INTENSIVE WRINKLE EYE
NDC: 69153-090 | Form: CREAM
Manufacturer: AN Co Ltd.
Category: otc | Type: HUMAN OTC DRUG LABEL
Date: 20160624

ACTIVE INGREDIENTS: Glycerin 8.81 g/25 g
INACTIVE INGREDIENTS: Water; Butylene Glycol

ACTIVE INGREDIENT

Active Ingredient: Glycerin 35.25%

INACTIVE INGREDIENT

Inactive Ingredients: Glyceryl Acrylate/Acrylic Acid Copolymer/Propylene Glycol, Water, Butylene Glycol, Panthenol, 1,2-Hexanediol, PEG-10 Dimethicone, Betaine, Cyclopentasiloxane/Cyclotetrasiloxane/Dimethiconol, Polysorbate 20, Phenyl Trimethicone, Beta-Glucan, Polyquaternium-51, CeramideNP/Hydrogenated Polydecene/Stearic Acid/ButyrospermumParkii(Shea) Butter/Ceteareth-20/Glyceryl Citrate/Lactate/Linoleate/Oleate Butylene glycol, Phenoxyethanol, Dipotassium Glycyrrhizate, Fragrance, PPG-26-Buteth-26/PEG-40 Hydrogenated Castor Oil, Hovenia Dulcis Fruit Extract, Aloe Barbadensis Leaf Extract, Copper Tripeptide-1, Palmitoyl Pentapeptide-4, Acetyl Hexapeptide-8

PURPOSE

Purpose: Skin Protectant

WARNINGS

Precautions on use: 1. Stop using the product if there are any of the following abnormal symptoms appearing after use and consult with your dermatologist as continued use can worsen the symptoms. A) If there are red spots, swelling, itchiness, or irritation B) If the above symptoms appear around the skin to which the product has been applied after being exposed to direct sunlight. 2. Precautions on storage and handling A) Make sure to close the cap after use. B) Keep out of the reach of children. C) Do not keep the product in a hot or cold place or a place getting direct sunlight. 3. Do not apply the product to any parts of the skin with wound, eczema, or dermatitis.

KEEP OUT OF REACH OF CHILDREN

Suggested use

Suggested use: After applying mask pack every morning and evening, apply to the skin around eye gently and evenly.

DOSAGE & ADMINISTRATION

Dosage & administration: Apply 1~2g of cream to the skin around eye once a day.